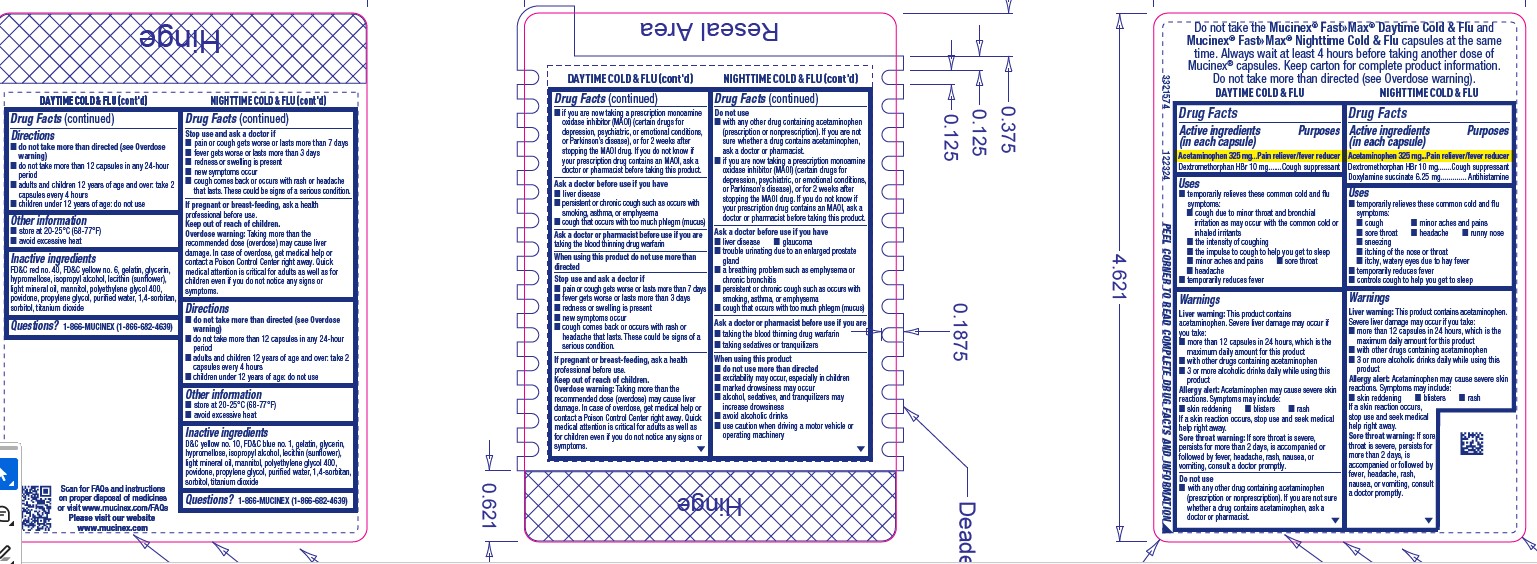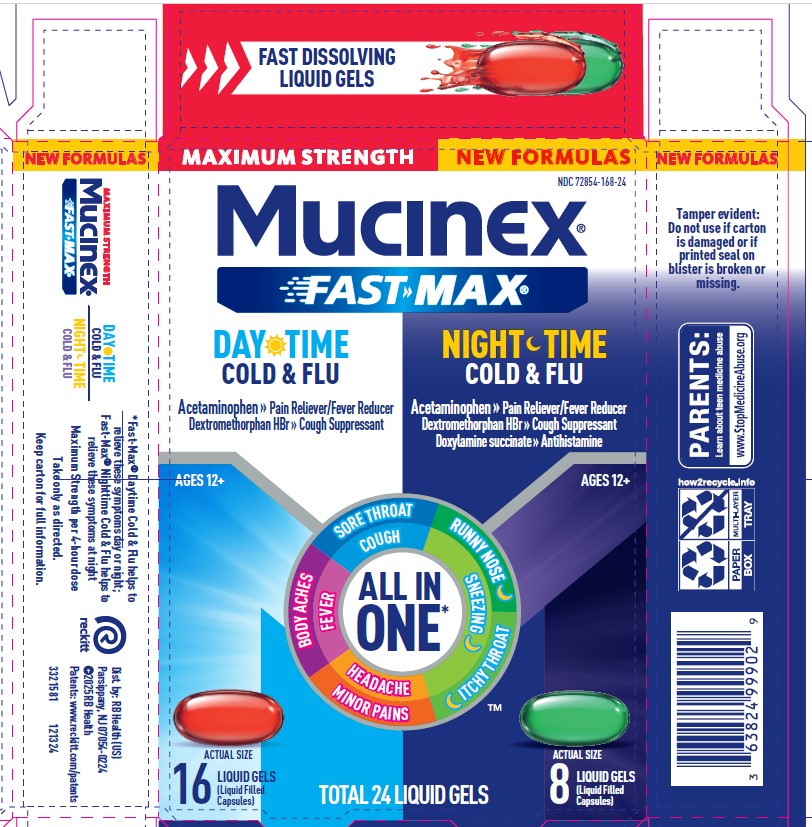 DRUG LABEL: MUCINEX FAST-MAX Liquid Gels Day Night Cold and Flu
NDC: 72854-168 | Form: KIT | Route: ORAL
Manufacturer: RB Health (US) LLC
Category: otc | Type: HUMAN OTC DRUG LABEL
Date: 20250624

ACTIVE INGREDIENTS: ACETAMINOPHEN 325 mg/1 1; DEXTROMETHORPHAN HYDROBROMIDE 10 mg/1 1; ACETAMINOPHEN 325 mg/1 1; DEXTROMETHORPHAN HYDROBROMIDE 10 mg/1 1; DOXYLAMINE SUCCINATE 6.25 mg/1 1
INACTIVE INGREDIENTS: FD&C RED NO. 40; GELATIN; LIGHT MINERAL OIL; MANNITOL; POLYETHYLENE GLYCOL 400; POVIDONE; WATER; HYPROMELLOSES; ISOPROPYL ALCOHOL; PROPYLENE GLYCOL; SORBITOL; FD&C YELLOW NO. 6; 1,4-SORBITAN; LECITHIN, SUNFLOWER; TITANIUM DIOXIDE; GLYCERIN; D&C YELLOW NO. 10; LIGHT MINERAL OIL; SORBITOL; 1,4-SORBITAN; POVIDONE; FD&C BLUE NO. 1; HYPROMELLOSES; POLYETHYLENE GLYCOL 400; GELATIN; GLYCERIN; MANNITOL; PROPYLENE GLYCOL; ISOPROPYL ALCOHOL; TITANIUM DIOXIDE; WATER; LECITHIN, SUNFLOWER

MUCINEX® FAST-MAX® Liquid Gels - Day Night Cold & Flu

Purpose Day:
Acetaminophen 325 mg...Pain reliever/fever reducer

Dextromethorphan HBr 10 mg.......Cough suppressant

Purpose Night:

Acetaminophen 325 mg...Pain reliever/fever reducer
Dextromethorphan HBr 10 mg.......Cough suppressant
Doxylamine succinate 6.25 mg............. Antihistamine

ACTIVE INGREDIENT

Day:

Acetaminophen 325 mg

Dextromethorphan HBr 10 mg

Night:

Acetaminophen 325 mg
Dextromethorphan HBr 10 mg
Doxylamine succinate 6.25 mg

INDICATIONS AND USAGE

Day:

■ temporarily relieves these common cold and flu
symptoms:
■ cough due to minor throat and bronchial
irritation as may occur with the common cold or
inhaled irritants
■ the intensity of coughing
■ the impulse to cough to help you get to sleep
■ minor aches and pains ■ sore throat
■ headache
■ temporarily reduces fever

Night:

■ temporarily relieves these common cold and flu
symptoms:
■ cough ■ minor aches and pains
■ sore throat ■ headache ■ runny nose
■ sneezing
■ itching of the nose or throat
■ itchy, watery eyes due to hay fever
■ temporarily reduces fever
■ controls cough to help you get to sleep

WARNINGS

Day:

Liver warning: This product contains
acetaminophen. Severe liver damage may occur if
you take:
■ more than 12 capsules in 24 hours, which is the
maximum daily amount for this product
■ with other drugs containing acetaminophen
■ 3 or more alcoholic drinks daily while using this
product

Allergy alert: Acetaminophen may cause severe skin
reactions. Symptoms may include:
■ skin reddening ■ blisters ■ rash
If a skin reaction occurs, stop use and seek medical
help right away.

Sore throat warning: If sore throat is severe,
persists for more than 2 days, is accompanied or
followed by fever, headache, rash, nausea, or
vomiting, consult a doctor promptly.

Do not use
■ with any other drug containing acetaminophen
(prescription or nonprescription). If you are not sure
whether a drug contains acetaminophen, ask a
doctor or pharmacist.

■ if you are now taking a prescription monoamine
oxidase inhibitor (MAOI) (certain drugs for
depression, psychiatric, or emotional conditions,
or Parkinson’s disease), or for 2 weeks after
stopping the MAOI drug. If you do not know if
your prescription drug contains an MAOI, ask a
doctor or pharmacist before taking this product.

Ask a doctor before use if you have
■ liver disease
■ persistent or chronic cough such as occurs with
smoking, asthma, or emphysema
■ cough that occurs with too much phlegm (mucus)
Ask a doctor or pharmacist before use if you are
taking the blood thinning drug warfarin

When using this product do not use more than
directed

Stop use and ask a doctor if
■ pain or cough gets worse or lasts more than 7 days
■ fever gets worse or lasts more than 3 days
■ redness or swelling is present
■ new symptoms occur
■ cough comes back or occurs with rash or
headache that lasts. These could be signs of a
serious condition.
Overdose warning: Taking more than the
recommended dose (overdose) may cause liver
damage. In case of overdose, get medical help or
contact a Poison Control Center right away. Quick
medical attention is critical for adults as well as
for children even if you do not notice any signs or
symptoms.

Night:

Severe liver damage may occur if you take:
■ more than 12 capsules in 24 hours, which is the
maximum daily amount for this product
■ with other drugs containing acetaminophen
■ 3 or more alcoholic drinks daily while using this
product

Allergy alert: Acetaminophen may cause severe skin
reactions. Symptoms may include:
■ skin reddening ■ blisters ■ rash
If a skin reaction occurs,
stop use and seek medical
help right away.

Sore throat warning: If sore
throat is severe, persists for
more than 2 days, is
accompanied or followed by
fever, headache, rash,
nausea, or vomiting, consult
a doctor promptly.

Do not use
■ with any other drug containing acetaminophen
(prescription or nonprescription). If you are not
sure whether a drug contains acetaminophen,
ask a doctor or pharmacist.
■ if you are now taking a prescription monoamine
oxidase inhibitor (MAOI) (certain drugs for
depression, psychiatric, or emotional conditions,
or Parkinson’s disease), or for 2 weeks after
stopping the MAOI drug. If you do not know if
your prescription drug contains an MAOI, ask a
doctor or pharmacist before taking this product.

Ask a doctor before use if you have
■ liver disease ■ glaucoma
■ trouble urinating due to an enlarged prostate
gland
■ a breathing problem such as emphysema or
chronic bronchitis
■ persistent or chronic cough such as occurs with
smoking, asthma, or emphysema
■ cough that occurs with too much phlegm (mucus)
Ask a doctor or pharmacist before use if you are
■ taking the blood thinning drug warfarin
■ taking sedatives or tranquilizers

When using this product
■ do not use more than directed
■ excitability may occur, especially in children
■ marked drowsiness may occur
■ alcohol, sedatives, and tranquilizers may
increase drowsiness
■ avoid alcoholic drinks
■ use caution when driving a motor vehicle or
operating machinery

DOSAGE AND ADMINISTRATION

Day:

Directions
■ do not take more than directed (see Overdose
warning)
■ do not take more than 12 capsules in any 24-hour
period
■ adults and children 12 years of age and over: take 2
capsules every 4 hours
■ children under 12 years of age: do not use

Night:

Directions
■ do not take more than directed (see Overdose
warning)
■ do not take more than 12 capsules in any 24-hour
period
■ adults and children 12 years of age and over: take 2
capsules every 4 hours
■ children under 12 years of age: do not use

Other information
■ store at 20-25°C (68-77°F)
■ avoid excessive heat

KEEP OUT OF REACH OF CHILDREN

If pregnant or breast-feeding, ask a health
professional before use.

Keep out of reach of children.

Overdose warning: Taking more than the
recommended dose (overdose) may cause liver
damage. In case of overdose, get medical help or
contact a Poison Control Center right away. Quick
medical attention is critical for adults as well as for
children even if you do not notice any signs or
symptoms.

INACTIVE INGREDIENT

Day:

FD&C red no. 40, FD&C yellow no. 6, gelatin, glycerin,
hypromellose, isopropyl alcohol, lecithin (sunflower),
light mineral oil, mannitol, polyethylene glycol 400,
povidone, propylene glycol, purified water, 1,4-sorbitan,
sorbitol, titanium dioxide

Night:

D&C yellow no. 10, FD&C blue no. 1, gelatin, glycerin,
hypromellose, isopropyl alcohol, lecithin (sunflower),
light mineral oil, mannitol, polyethylene glycol 400,
povidone, propylene glycol, purified water, 1,4-sorbitan,
sorbitol, titanium dioxide

Questions? 1-866-MUCINEX (1-866-682-4639)